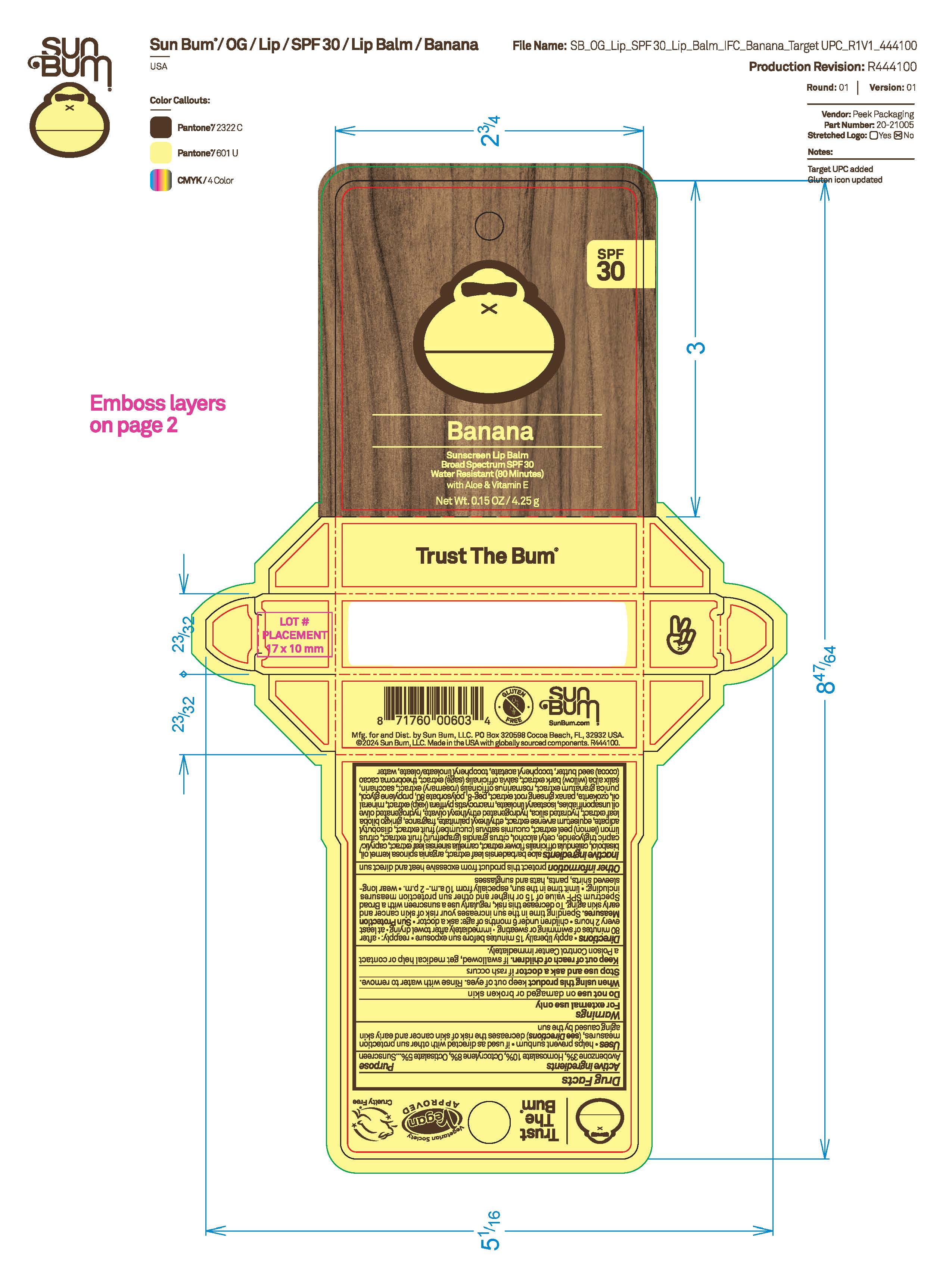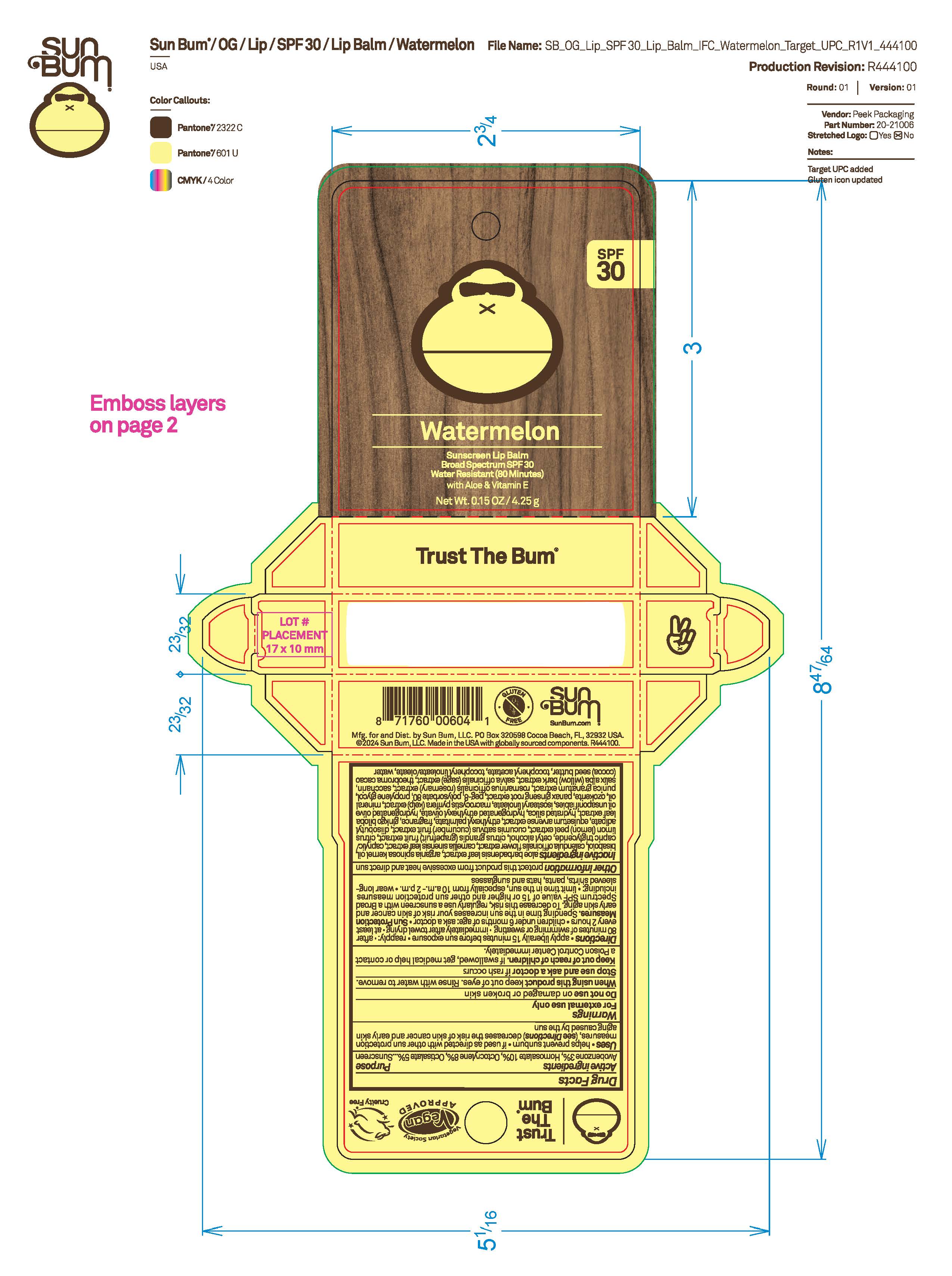 DRUG LABEL: Lip Balm - Variety Pack (Target) - Watermelon (8)
NDC: 69039-809 | Form: STICK
Manufacturer: Sun Bum, LLC
Category: otc | Type: HUMAN OTC DRUG LABEL
Date: 20250819

ACTIVE INGREDIENTS: AVOBENZONE 30 mg/1 g; HOMOSALATE 100 mg/1 g; OCTISALATE 80 mg/1 g; OCTOCRYLENE 50 mg/1 g
INACTIVE INGREDIENTS: BISABOLOL; DIISOBUTYL ADIPATE; CAPRYLIC/CAPRIC TRIGLYCERIDE; GINKGO BILOBA LEAF; CETYL ALCOHOL; GRAPEFRUIT; CITRUS LIMON (LEMON) PEEL; HYDRATED SILICA; WILLOW BARK; .ALPHA.-TOCOPHEROL ACETATE; .ALPHA.-TOCOPHEROL LINOLEATE, D-; CALENDULA OFFICINALIS FLOWER; EQUISETUM ARVENSE WHOLE; HYDROGENATED OLIVE OIL UNSAPONIFIABLES; PEG-8; CERESIN; POLYSORBATE 80; PROPYLENE GLYCOL; SAGE; HYDROGENATED ETHYLHEXYL OLIVATE; WATER; SACCHARIN; THEOBROMA CACAO (COCOA) SEED BUTTER; CUCUMIS SATIVUS (CUCUMBER) FRUIT; ISOSTEARYL LINOLEATE; PUNICA GRANATUM WHOLE; PANAX GINSENG ROOT; ROSEMARY; CAMELLIA SINENSIS LEAF; ARGANIA SPINOSA KERNEL OIL; ETHYLHEXYL OLIVATE; MACROCYSTIS PYRIFERA (KELP); MINERAL OIL; ALOE BARBADENSIS LEAF

Lip Balm - Variety Pack (Target) - Banana, Watermelon

Active Ingredients

AVOBENZONE 3%, HOMOSALATE 10%, OCTISALATE 8%, OCTOCRYLENE 5%

Purpose

Sunscreen

Uses

• helps prevent sunburn • if used as directed with other sun protection measures, (see Directions) decreases the risk of skin cancer and early skin aging caused by the sun

Warnings

For external use only

Do not use on damaged or broken skin

When using this product keep out of eyes. Rinse with water to remove.

Stop use and ask a doctor if rash occurs

Keep out of reach of children. If swallowed, get medical help or contact a Poison Control Center immediately.

Warnings

Keep Out Of Reach Of Children

Directions

• apply liberally 15 minutes before sun exposure

• reapply: • after 80 minutes of swimming or sweating • immediately after towel drying • at least every 2 hours

• children under 6 months of age: ask a doctor

• Sun Protection Measures. Spending time in the sun increases your risk of skin cancer and early skin aging. To decrease this risk, regularly use a sunscreen with a Broad Spectrum SPF value of 15 or higher and other sun protection measures including:

• limit time in the sun, especially from 10 a.m.- 2 p.m.

• wear long-sleeved shirts, pants, hats and sunglasses

Directions

• apply liberally 15 minutes before sun exposure

Other Information

protect this product from excessive heat and direct sun

Inactive Ingredients

aloe barbadensis leaf extract, argania spinosa kernel oil, bisabolol, calendula officinalis flower extract, caprylic/capric triglyceride, cetyl alcohol, citrus grandis (grapefruit) fruit extract, citrus limon (lemon) peel extract, cucumis sativus (cucumber) fruit extract, diisobutyl adipate, equisetum arvense extract, ethylhexyl palmitate, fragrance, ginkgo biloba leaf extract, hydrated silica, hydrogenated ethylhexyl olivate, hydrogenated olive oil unsaponifiables, isostearyl linoleate, macrocystis pyrifera (kelp) extract, mineral oil, ozokerite, panax ginseng root extract, peg-8, polysorbate 80, propylene glycol, punica granatum extract, rosmarinus officinalis (rosemary) extract, saccharin, salix alba (willow) bark extract, salvia officinalis (sage) extract, theobroma cacao (cocoa) seed butter, tocopheryl acetate, tocopheryl linoleate/oleate, water

Questions?

1-877-978-6286